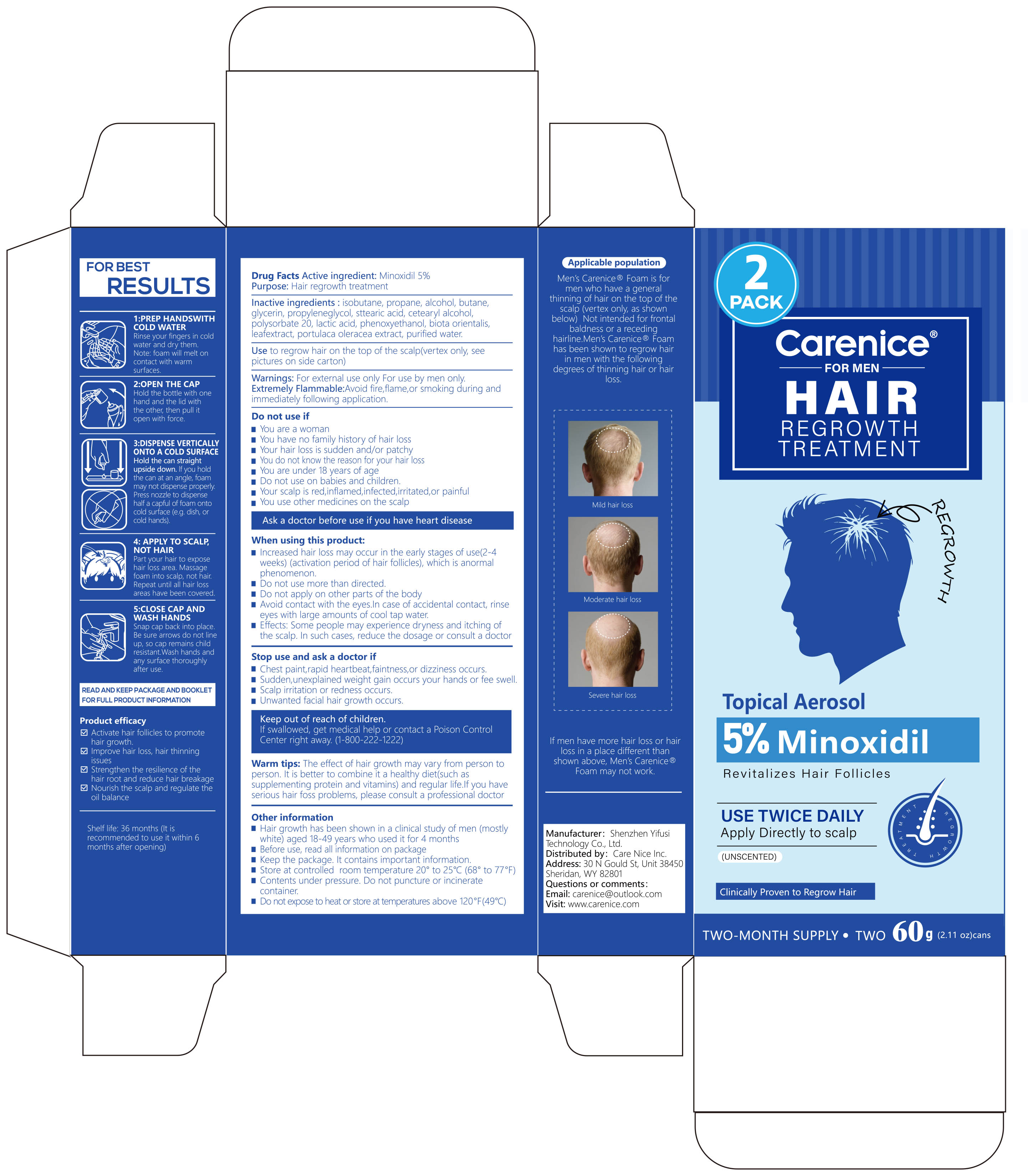 DRUG LABEL: Carenice 5% Minoxidil HAIR REGROWTH TREATMENT
NDC: 87086-001 | Form: AEROSOL, FOAM
Manufacturer: Shenzhen Yifusi Technology Co., Ltd.
Category: otc | Type: HUMAN OTC DRUG LABEL
Date: 20250907

ACTIVE INGREDIENTS: MINOXIDIL 5 g/100 g
INACTIVE INGREDIENTS: PHENOXYETHANOL; STEARIC ACID; CAMELLIA SINENSIS LEAF; GLYCERIN; PROPANE; ISOBUTANE; LACTIC ACID; BUTANE; POLYSORBATE 20; PLATYCLADUS ORIENTALIS WHOLE; WATER; PURSLANE; ALCOHOL; PROPYLENE GLYCOL; CETEARYL ALCOHOL

87086-001 Carenice 5% Minoxidil HAIR REGROWTH TREATMENT

ACTIVE INGREDIENT

MINOXIDIL 5%

PURPOSE

Hair regrowth treatment

INDICATIONS AND USAGE

Use to regrow hair on the top of the scalp(vertex only, see pictures on side carton)

WARNINGS

For external use only For use by men only
Extremely Flammable:Avoid fire,flame,or smoking during and immediately following application.

DO NOT USE

You are a woman
You have no family history of hair loss
Your hair loss is sudden and/or patchy
You do not know the reason for your hair loss
You are under 18 years of age
Do not use on babies and children
Your scalp is red,inflamed,infected,irritated,or painful
You use other medicines on the scalp

WHEN USING

Increased hair loss may occur in the early stages of use(2-4 weeks) (activation period of hair follicles), which is anormalohenomenon.
Do not use more than directed.
Do not apply on other parts of the body
Avoid contact with the eyes.In case of accidental contact, rinse eyes with large amounts of cool tap water.
Effects: Some people may experience dryness and itching of the scalp. In such cases, reduce the dosage or consult a doctor

STOP USE

Chest paint,rapid heartbeat,faintness,or dizziness occurs.
Sudden,unexplained weight gain occurs your hands or fee swell
Scalp irritation or redness occurs.
Unwanted facial hair growth occurs.

Keep out of reach of children.If swallowed, get medical help or contact a Poison ControlCenter right away. (1-800-222-1222)

DOSAGE AND ADMINISTRATION

1:PREP HANDSWITHCOLD WATER
Rinse your fingers in cold water and dry them.
Note: foam will melt oncontact with warmsurfaces.
2:OPEN THE CAP
Hold the bottle with one hand and the lid with the other, then pull it open with force.
3:DISPENSE VERTICALLYONTO A COLD SURFACE
Hold the can straight
upside down. lf you hold the can at an angle, foam may not dispense properly.Press nozzle to dispense half a capful of foam onto cold surface (e.g. dish, or cold hands).
4: APPLY TO SCALPNOT HAIR
Part your hair to expose hair loss area. Massage foam into scalp, not hair.Repeat until all hair loss areas have been covered.
5:CLOSE CAP ANDWASH HANDS
Snap cap back into place.Be sure arrows do not line up, so cap remains child resistant.Wash hands and any surface thoroughly after use.

INACTIVE INGREDIENT

Inactive ingredients : isobutane, propane, alcohol, butane,glycerin, propyleneglycol, sttearic acid, cetearyl alcohol,polysorbate 20, lactic acid, phenoxyethanol, biota orientalis,leafextract, portulaca oleracea extract, purified water.